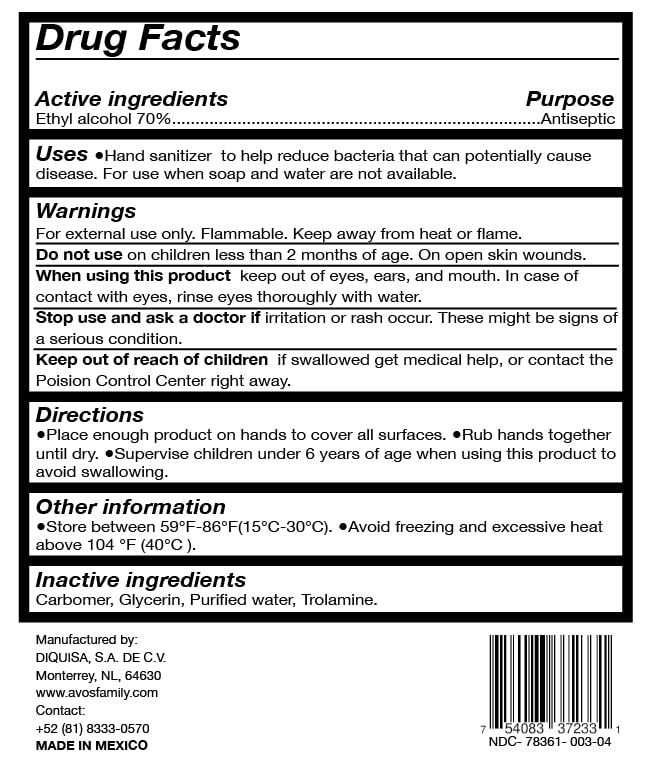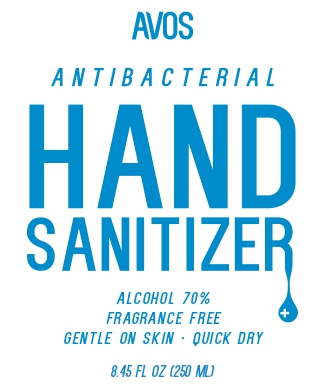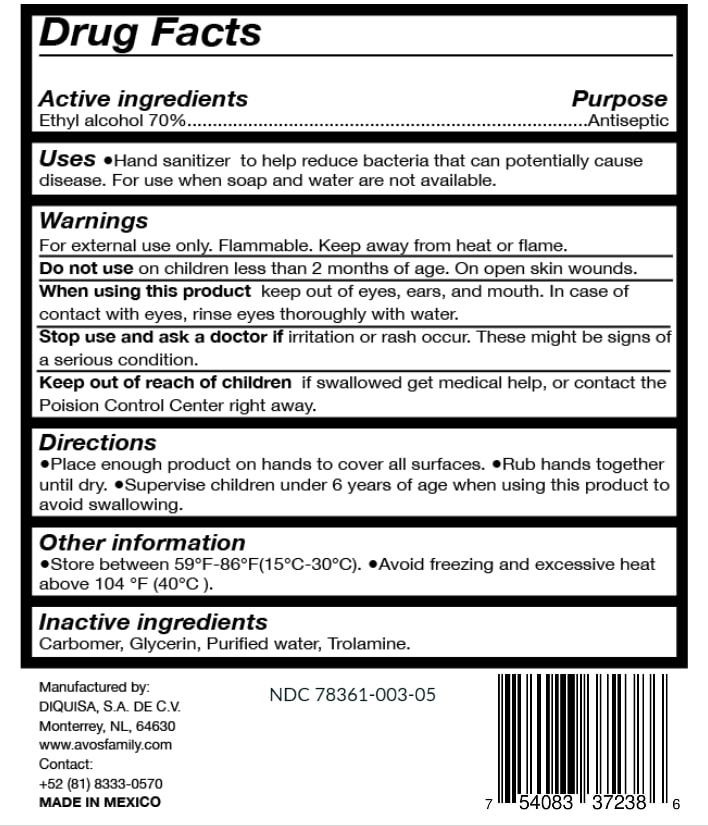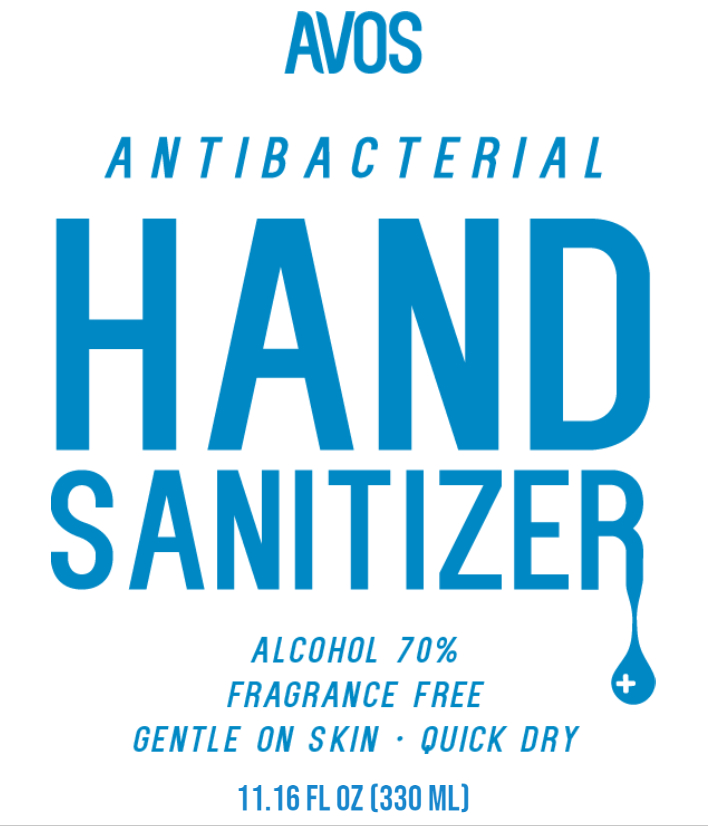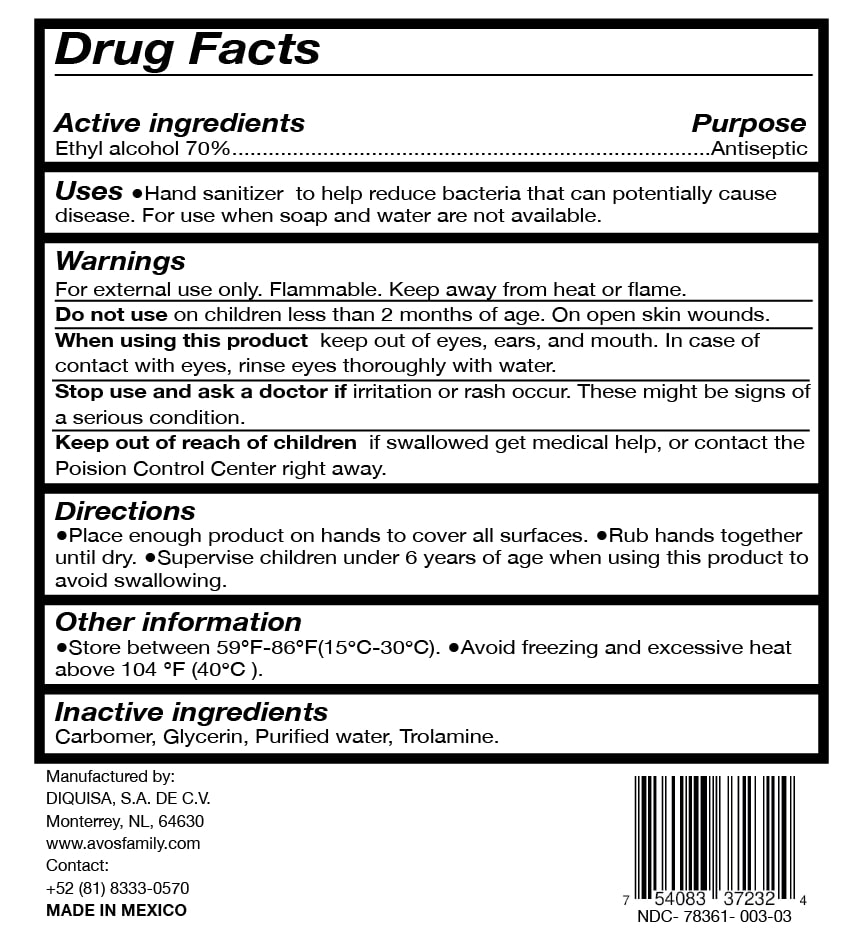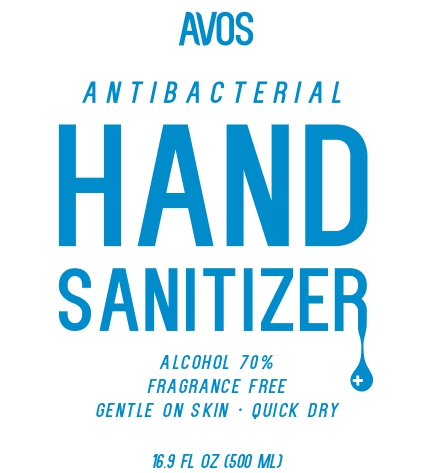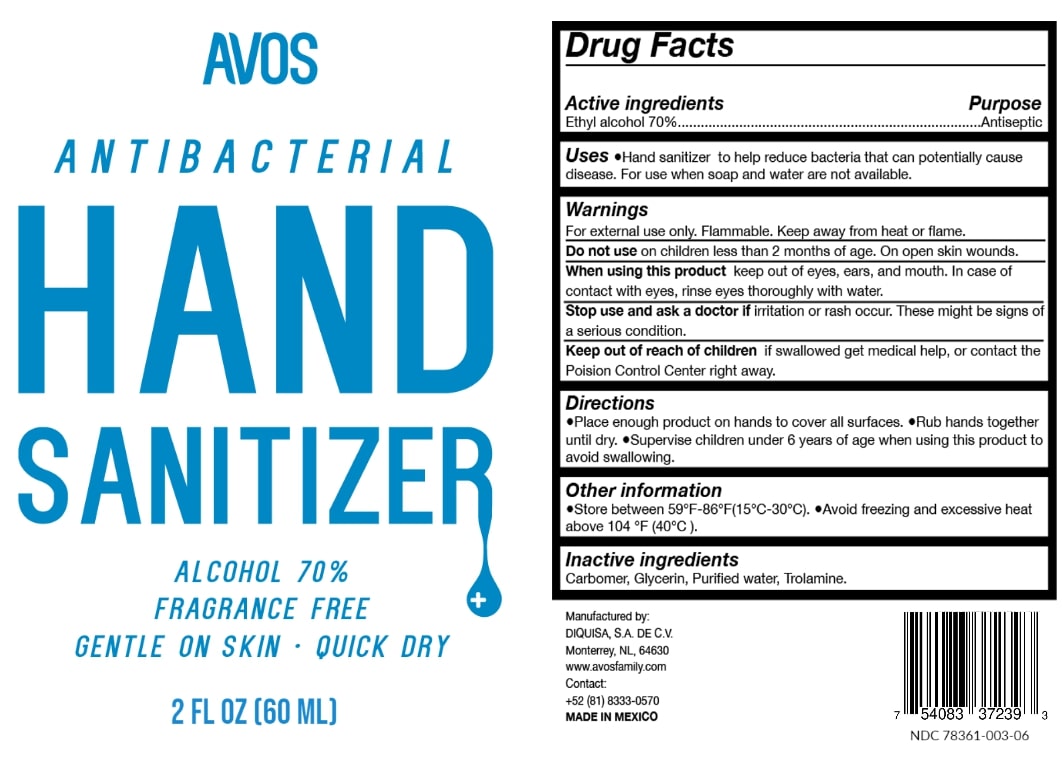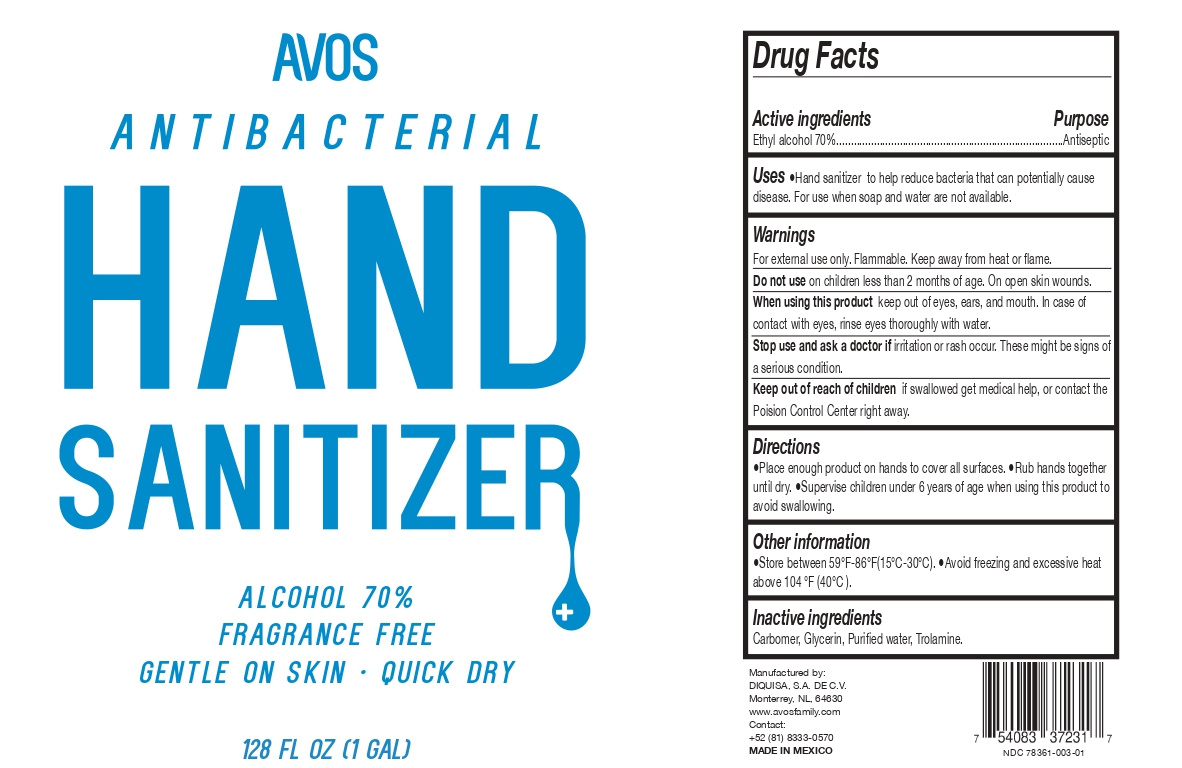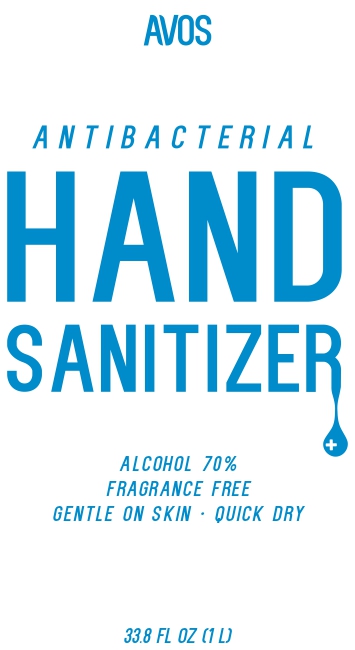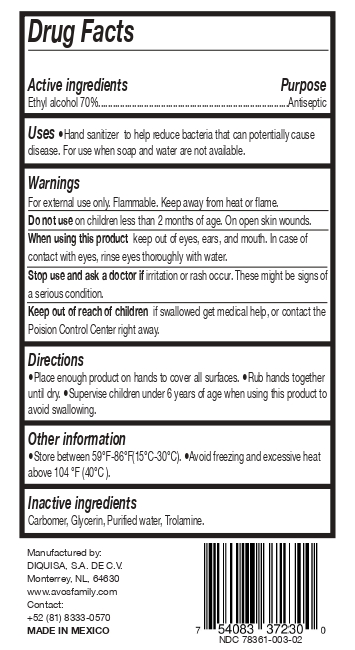 DRUG LABEL: Hand Sanitizer
NDC: 78361-003 | Form: GEL
Manufacturer: Diquisa, S.A. De C.V.
Category: otc | Type: HUMAN OTC DRUG LABEL
Date: 20200806

ACTIVE INGREDIENTS: ALCOHOL 70 mL/100 mL
INACTIVE INGREDIENTS: TROLAMINE 0.1 mL/100 mL; WATER; CARBOMER HOMOPOLYMER, UNSPECIFIED TYPE 0.4 mL/100 mL; GLYCERIN 0.5 mL/100 mL

Hand Sanitizer

Active Ingredient(s)

Ethyl Alcohol 70% v/v.

Purpose

Antiseptic

Use

Hand Sanitizer to help reduce bacteria that potentially can cause disease. For use when soap and water are not available.

Warnings

For external use only. Flammable. Keep away from heat or flame

Do not use

- on children less than 2 months of age
- on open skin wounds

When using this product keep out of eyes, ears, and mouth. In case of contact with eyes, rinse eyes thoroughly with water.

Stop use and ask a doctor if irritation or rash occurs. These may be signs of a serious condition.

Keep out of reach of children. If swallowed, get medical help or contact a Poison Control Center right away.

Directions

- Place enough product on hands to cover all surfaces. Rub hands together until dry.
- Supervise children under 6 years of age when using this product to avoid swallowing.

Other information

- Store between 59ºF-86ºF (15ºC-30ºC)
- Avoid freezing and excessive heat above 104ºF (40ºC)

Inactive ingredients

Carbomer, Glycerin, Purified water, Trolamine

Package Label - Principal Display Panel

3780 mL NDC: 78361-003-01
1000 mL NDC: 78361-003-02
500 mL NDC: 78361-003-03
250 mL NDC: 78361-003-04
330 mL NDC: 78361-003-05
60 mL NDC: 78361-003-06